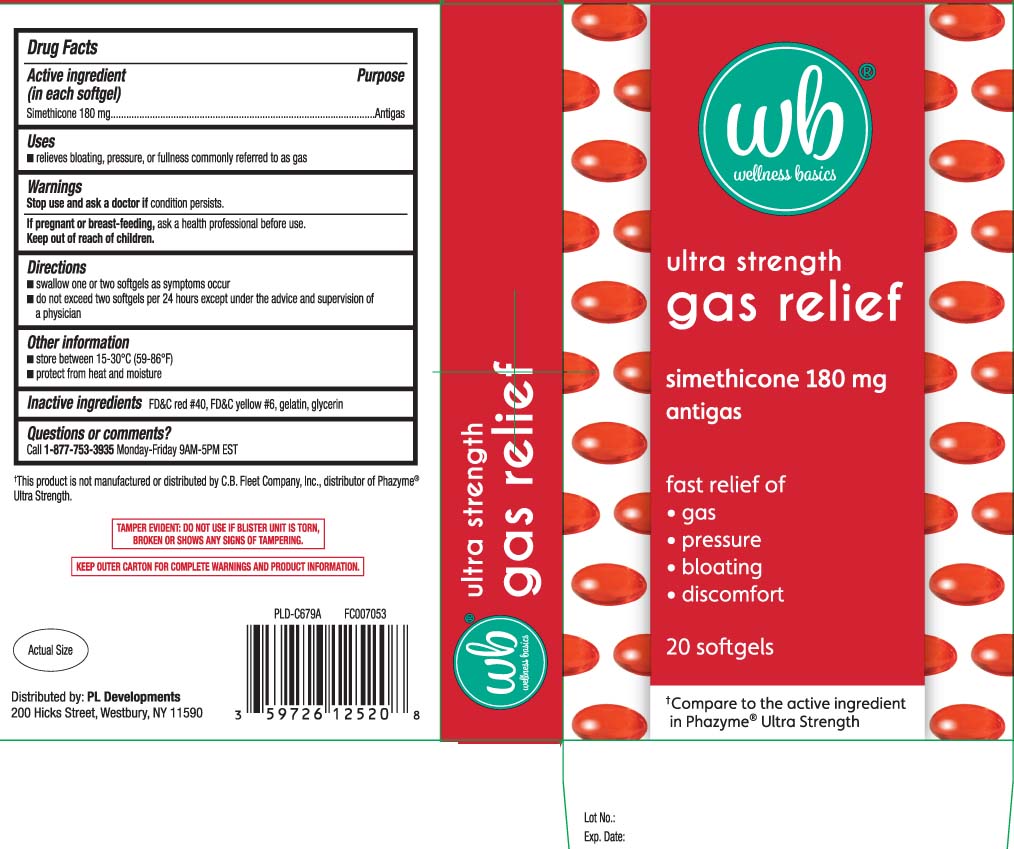 DRUG LABEL: Gas Relief
NDC: 59726-773 | Form: CAPSULE, LIQUID FILLED
Manufacturer: P & L Development, LLC
Category: otc | Type: HUMAN OTC DRUG LABEL
Date: 20251117

ACTIVE INGREDIENTS: DIMETHICONE 180 mg/1 1
INACTIVE INGREDIENTS: FD&C YELLOW NO. 6; GELATIN; GLYCERIN; FD&C RED NO. 40

Drug Facts

Active ingredient (in each softgel)

Simethicone 180 mg

Purpose

Antigas

Uses

- relieves bloating, pressure, or fullness commonly referred to as gas

Warnings

Stop use and ask a doctor if

condition persists.

If pregnant or breast-feeding,

ask a health professional before use.

Directions

- swallow one or two softgels as needed after meals
- do not exceed two softgels per day except under the advice and supervision of a physician

Other information

- store between 15-30ºC (59-86ºF)
- protect from heat and moisture

Inactive ingredients

FD&C red #40*, FD&C yellow #6, gelatin, glycerin

Questions or comments?

Call 1-877-753-3935 Monday-Friday 9AM-5PM EST

Principal Display Panel

†Compare to the active ingredient in Phazyme® Ultra Strength

ultra strength

gas relief

simethicone 180 mg

antigas

fast relief of

- gas
- pressure
- bloating
- discomfort

softgels

†This product is not manufactured or distributed by C.B. Fleet Company Inc., distributor of Phazyme® Ultra Strength

TAMPER EVIDENT: DO NOT USE IF BLISTER UNIT IS TORN, BROKEN OR SHOWS ANY SIGNS OF TAMPERING.

KEEP OUTER CARTON FOR COMPLETE WARNINGS AND PRODUCT INFORMATION.

Distributed by: PL Developments

200 Hicks Street, Westbury, NY 11590

Product Label

WELLNESS BASICS Ultra Strength Gas Relief